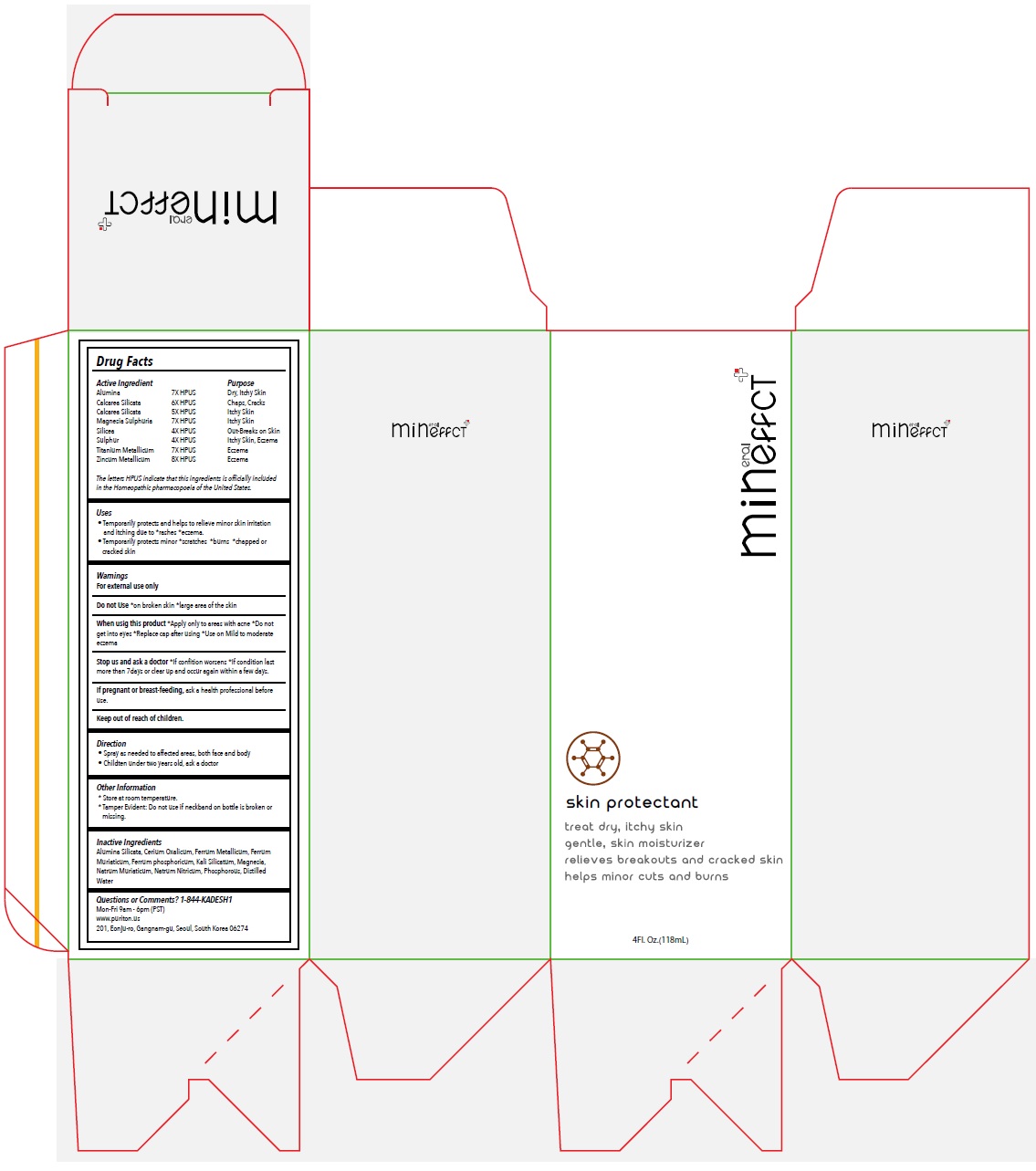 DRUG LABEL: Mineffect skin protectant
NDC: 81488-002 | Form: SPRAY
Manufacturer: Kadesh Incoporation Co,Ltd
Category: homeopathic | Type: HUMAN OTC DRUG LABEL
Date: 20231031

ACTIVE INGREDIENTS: ALUMINUM OXIDE 7 [hp_X]/118 mL; CALCIUM SILICATE 6 [hp_X]/118 mL; MAGNESIUM SULFATE HEPTAHYDRATE 7 [hp_X]/118 mL; SILICON DIOXIDE 4 [hp_X]/118 mL; SULFUR 4 [hp_X]/118 mL; TITANIUM 7 [hp_X]/118 mL; ZINC 8 [hp_X]/118 mL
INACTIVE INGREDIENTS: KAOLIN; CEROUS OXALATE NONAHYDRATE; IRON; FERRIC CHLORIDE HEXAHYDRATE; FERROSOFERRIC PHOSPHATE; POTASSIUM SILICATE; MAGNESIUM CHLORIDE; SODIUM CHLORIDE; SODIUM NITRATE; PHOSPHORUS; WATER

Mineffect skin protectant

Active Ingredient

Alumina 7X HPUS
Calcarea Silicata 6X HPUS
Calcarea Silicata 5X HPUS
Magnesia Sulphurica 7X HPUS
Silicea 4X HPUS
Sulphur 4X HPUS
Titanium Metallicum 7X HPUS
Zincum Metallicum 8X HPUS

The letters HPUS indicate that this ingredients is officially included in the Homeopathic pharmacopoeia of the United States.

Purpose

Dry, Itchy Skin
Chaps, Cracks
Itchy Skin
Itchy Skin
Out-Breaks on Skin
Itchy Skin, Eczema
Eczema
Eczema

Uses

• Temporarily protects and helps to relieve minor skin irritation and itching due to *rashes *eczema.
• Temporarily protects minor *scratches *burns *chapped or cracked skin

Warnings

For external use only
Do not Use*on broken skin *large area of the skin
When using this product*Apply only to areas with acne *Do not get into eyes *Replace cap after using *Use on Mild to moderate eczema
Stop use and ask a doctor*If condition worsens *If condition last more than 7days or clear up and occur again within a few days.
If pregnant or breast-feeding, ask a health professional before use.

Keep out of reach of children.

Direction

• Spray as needed to affected areas, both face and body
• Children under two years old, ask a doctor

Other Information

* Store at room temperature.
* Tamper Evident: Do not use if neckband on bottle is broken or missing.

Inactive Ingredients

Alumina Silicata, Cerium Oxalicum, Ferrum Metallicum, Ferrum Muriaticum, Ferrum phosphoricum, Kali Silicatum, Magnesia, Natrum Muriaticum, Natrum Nitricum, Phosphorous, Distilled Water

Questions or Comments? 1-844-KADESH1

Mon-Fri 9am - 6pm (PST)
www.puriton.us
201, Eonju-ro, Gangnam-gu, Seoul, South Korea 06274

treat dry, itchy skin

gentle, skin moisturizer

relieves breakouts and cracked skin

helps minor cuts and burns